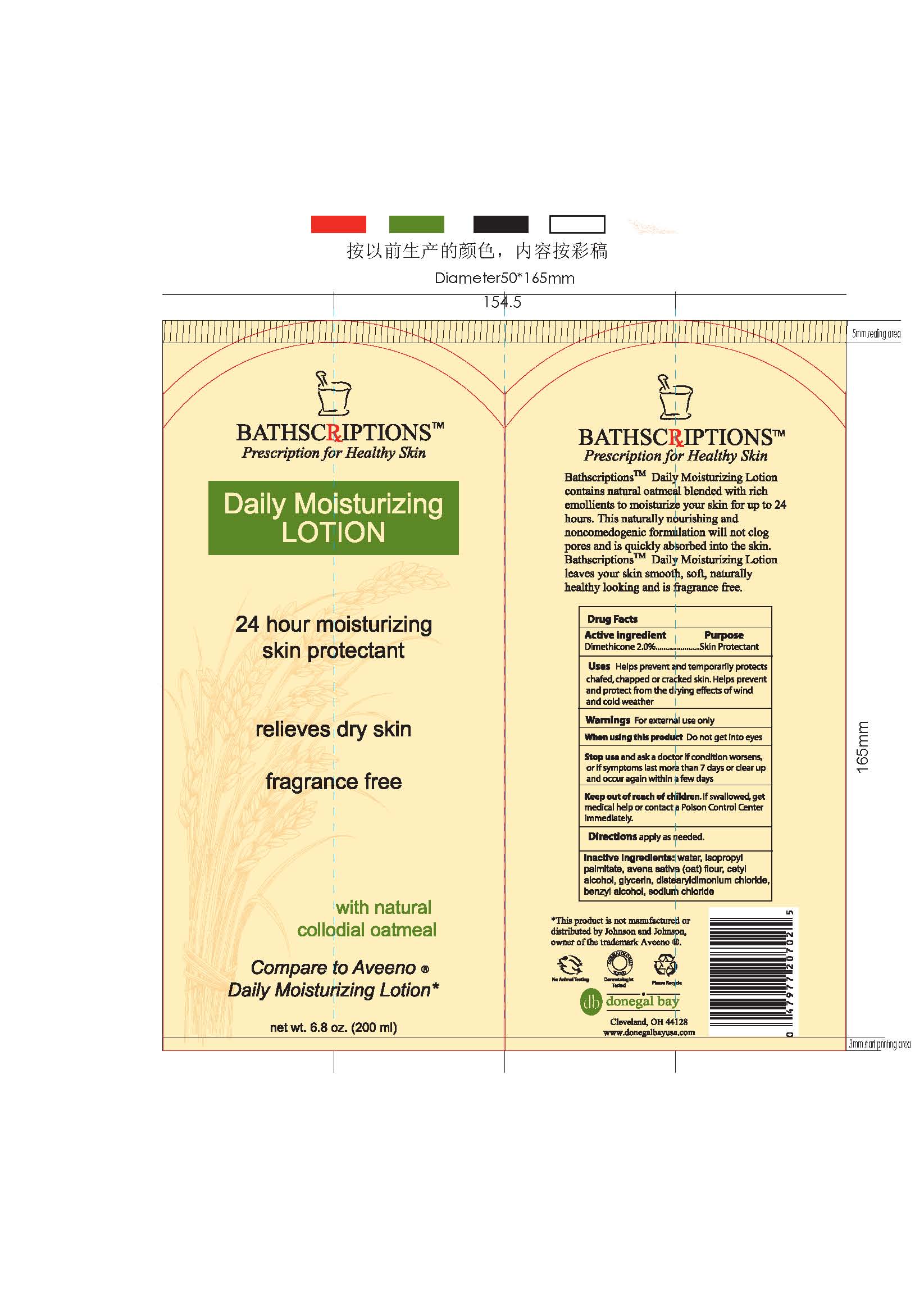 DRUG LABEL: Bathscriptions Daily Moisturizing
NDC: 70990-001 | Form: LOTION
Manufacturer: Donegal Bay Ltd
Category: otc | Type: HUMAN OTC DRUG LABEL
Date: 20161012

ACTIVE INGREDIENTS: DIMETHICONE 2 g/100 mL
INACTIVE INGREDIENTS: WATER; ISOPROPYL PALMITATE; CETYL ALCOHOL; GLYCERIN; BENZYL ALCOHOL; SODIUM CHLORIDE

Daily Moisturizing Lotion

Active Ingredient:

Dimethicone 2.0%

Purpose:

Skin Protectant

Uses:

Helps prevent and temporarily protects chafted, chapped or cracked skin. Helps prevent and protect from the drying effect of wind and cold weather

Warnings:

For external use only

When using this product, do not get into eyes

Stop use and ask a doctor if condition worsens or if symptoms last for more than 7 days or clear up and occur again within a few days

Keep out of reach of children. If swallowed, get medical help or contact a Poison Control Center immediately

DOSAGE AND ADMINISTRATION

Direction:

Apply as needed

Inactive Ingredients:

Water, Isopropyl Palmitate, Avena sativa (Oat) Flour, Cetyl Alcohol, Glycerin, Distearyldimonium Chloride, Benzyl Alcohol, Sodium Chloride